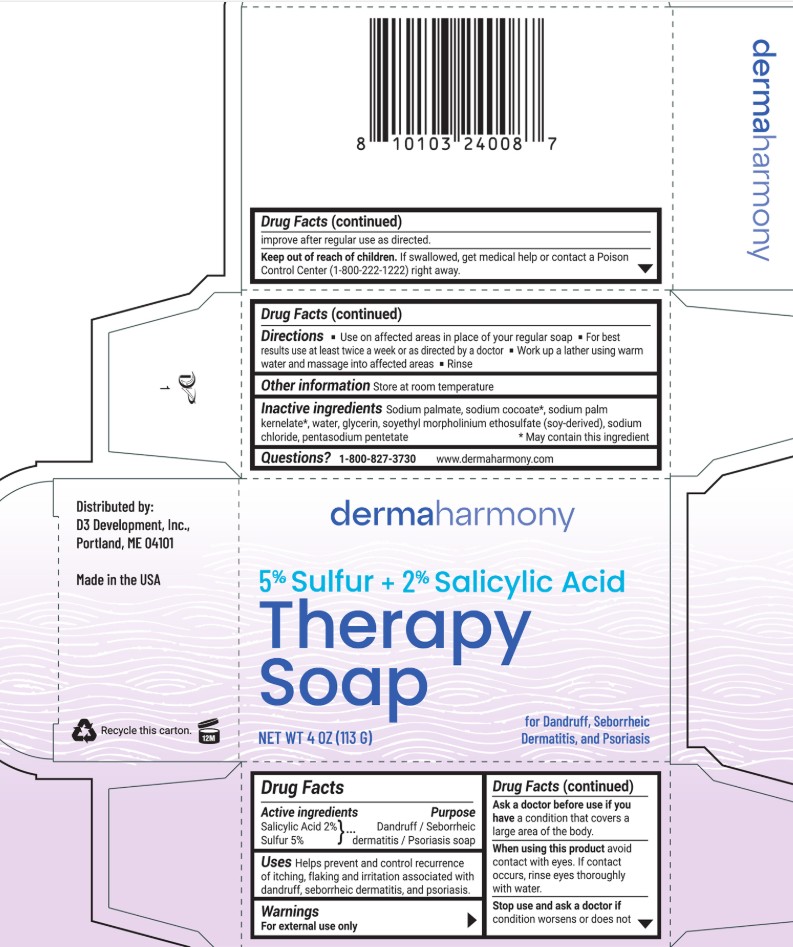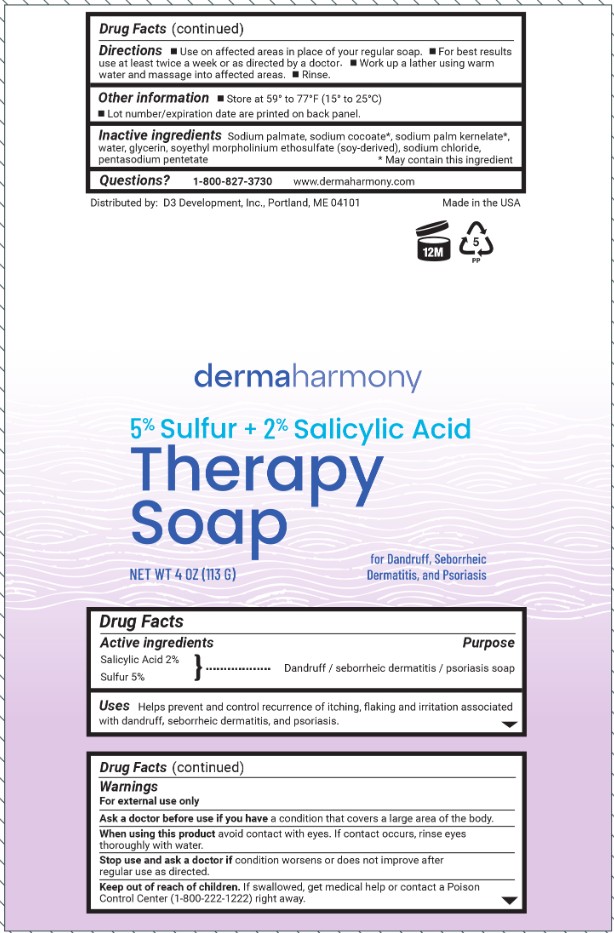 DRUG LABEL: Dermaharmony Sulfur and Salicylic Acid
NDC: 71819-004 | Form: SOAP
Manufacturer: D3 Development, Inc.
Category: otc | Type: HUMAN OTC DRUG LABEL
Date: 20251202

ACTIVE INGREDIENTS: SULFUR 5 g/100 g; SALICYLIC ACID 2 g/100 g
INACTIVE INGREDIENTS: SODIUM CHLORIDE; WATER; SODIUM COCOATE; GLYCERIN; SODIUM PALM KERNELATE; SODIUM PALMATE; SOYETHYL MORPHOLINIUM ETHOSULFATE; PENTASODIUM PENTETATE

Dermaharmony Sulfur and Salicylic Acid Soap

Drug Facts

Active ingredients

Salicylic acid 2%

Sulfur 5%

Purpose

Dandruff / sebhorreic dermatitis / psoriasis soap

Uses

Helps prevent and control recurrence of itching, flaking and irritation associated with dandruff, sebhorreic dermatitis, and psoriasis

Warnings

For external use only

Ask a doctor before use if you havea condition that covers a large area of the body.

When using this product,avoid contact with eyes. If contact occurs, rinse eyes thoroughly with water.

Stop use and ask a doctor ifcondition worsens or does not improve after regular use as directed.

Keep out of reach of children.If swallowed, get medical help or contact a Poison Control Center (1-800-222-1222) right away.

Directions

- Use on affected areas in place of your regular soap.
- For best results use at least twice a week or as directed by a doctor.
- Work up a lather using warm water and massage into affected areas.
- Rinse.

Other information

- Store at 59° to 77°F (15° to 25°C)
- Lot number and expiration date are printed on back panel

Inactive ingredients

Sodium palmate, sodium cocoate*, sodium palm kernelate*, water, glycerin, soyethyl morpholinium ethosulfate (soy derived), sodium chloride, pentasodium pentetate

*May contain this ingredient

Questions?

1-800-827-3730

www.dermaharmony.com

Distributed by:

D3 Development, Inc., Portland, ME 04101

Made in the USA

PACKAGE LABEL

dermaharmony

5% Sulfur & 2% Salicylic Acid SOAP

For Dandruff, Sebhorreic Dermatitis & Psoriasis

NET WT 4 OZ (113 G)